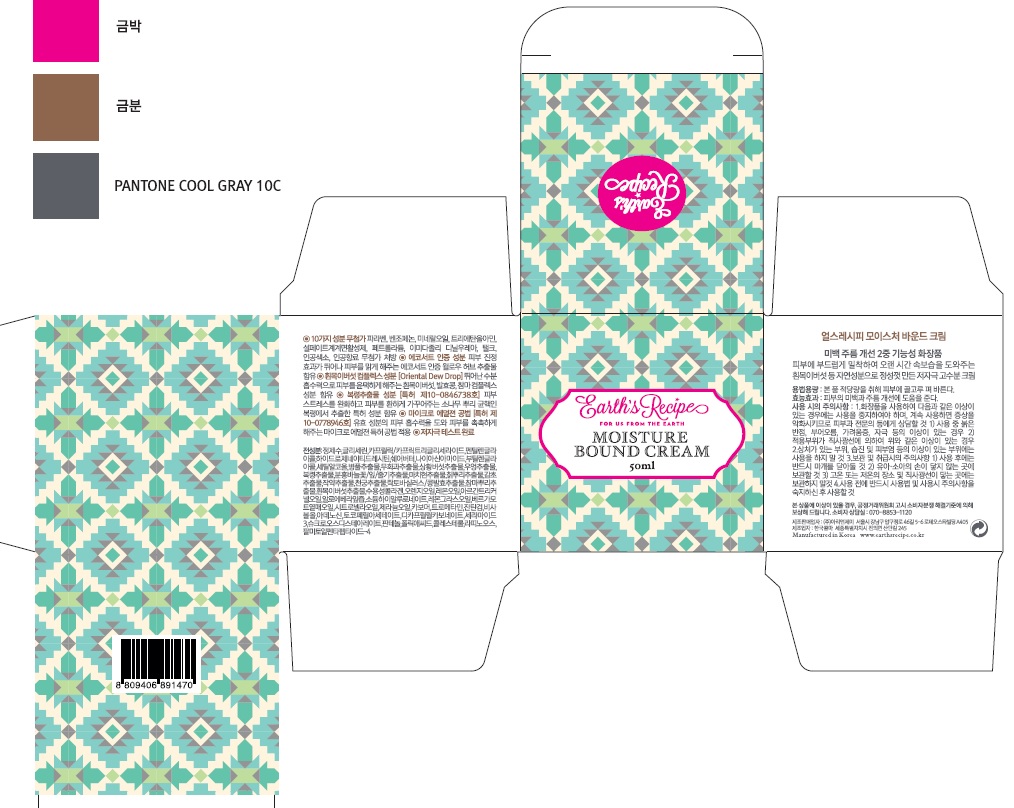 DRUG LABEL: Moisture Bound
NDC: 71496-0001 | Form: CREAM
Manufacturer: ARI&J Inc
Category: otc | Type: HUMAN OTC DRUG LABEL
Date: 20170704

ACTIVE INGREDIENTS: ADENOSINE 0.04 g/100 mL; TREMELLA FUCIFORMIS WHOLE 0.1 g/100 mL; CERAMIDE NP 0.01 g/100 mL; NIACINAMIDE 2 g/100 mL
INACTIVE INGREDIENTS: BUTYLENE GLYCOL; GLYCERIN; WATER

ACTIVE INGREDIENT

Tremella Fuciformis Whole, Niacinamide, Adenosine, Ceramide

INACTIVE INGREDIENT

Water, Glycerin, Butylene Glycol, etc

PURPOSE

Skin protectant - Anti Wrinkle, Whitening

Daily moisturizer that can be used day and night

keep out or reach of the children

INDICATIONS AND USAGE

After Cleansing your face, apply after applying serum.

Can be used as a mask when applied generously.

WARNINGS

- For external use only.
- Do not use on damaged or broken skin.
- If any signs of the following skin troubles apprear, stop use and talk yo your dermatologist.

1. Rash
2. Itching
3. Irritation

- Avoid placing this product in this container in the excessive heat or direct sun

DOSAGE AND ADMINISTRATION

for external use only